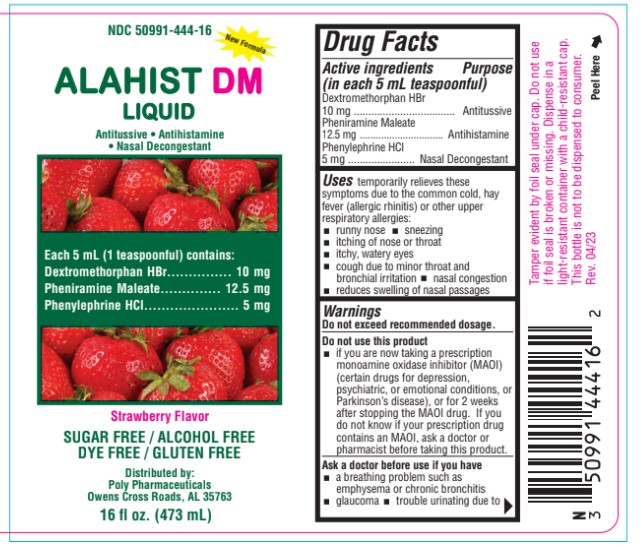 DRUG LABEL: ALAHIST DM
NDC: 50991-444 | Form: LIQUID
Manufacturer: Poly Pharmaceuticals, Inc.
Category: otc | Type: HUMAN OTC DRUG LABEL
Date: 20251203

ACTIVE INGREDIENTS: DEXTROMETHORPHAN HYDROBROMIDE 10 mg/5 mL; PHENYLEPHRINE HYDROCHLORIDE 5 mg/5 mL; PHENIRAMINE MALEATE 12.5 mg/5 mL
INACTIVE INGREDIENTS: PROPYLENE GLYCOL; WATER; PROPYLPARABEN; POTASSIUM CITRATE; CITRIC ACID MONOHYDRATE; SUCRALOSE; SORBITOL; METHYLPARABEN

ALAHIST DM

ALAHIST DM LIQUID

Drug Facts

Active ingredients

(in each 5 mL teaspoonful)
Dextromethorphan HBr............... 10 mg
Pheniramine Maleate.............. 12.5 mg
Phenylephrine HCl...................... 5 mg

Purpose

Antitussive

Antihistamine
Nasal Decongestant

Uses

temporarily relieves these symptoms due to the common cold, hay fever (allergic rhinitis) or other upper respiratory allergies:

- runny nose
- sneezing
- itching of nose or throat
- itchy, watery eyes
- cough due to minor throat and bronchial irritation
- nasal congestion
- reduces swelling of nasal passages

Warnings

Do not exceed recommended dosage.

Do not use

this product

- if you are now taking a prescription monoamine oxidase inhibitor (MAOI) (certain drugs for depression, psychiatric, or emotional conditions, or Parkinson's disease), or for 2 weeks after stopping the MAOI drug. If you do not know if your prescription drug contains an MAOI, ask a doctor or pharmacist before taking this product.

Ask a doctor before use

if you have

- a breathing problem such as emphysema or chronic bronchitis
- glaucoma
- trouble urinating due to an enlarged prostate gland
- a cough that lasts or is chronic such as occurs with smoking, asthma or emphysema
- a cough that occurs with too much phlegm (mucus)
- heart disease
- high blood pressure
- thyroid disease
- diabetes

Ask a doctor or pharmacist before use

if you are

taking sedatives or tranquilizers.

When using this product

- excitability may occur, especially in children
- may cause marked drowsiness
- avoid alcoholic drinks
- alcohol, sedatives, and tranquilizers may increase the drowsiness effect
- be careful when driving a motor vehicle or operating machinery

If pregnant or breast-feeding,

ask a health professional before use.

Keep out of reach of children.

In case of overdose, get medical help or contact a Poison Control Center right away.

Directions

Do not exceed recommended dosage.

Adults and children 12 years of age and over: | 2 teaspoonful (10 mL) every 4 to 6 hours, not to exceed 12 teaspoonfuls in a 24 hours
Children 6 to under 12 years of age: | 1 teaspoonful (5 mL) every 4 to 6 hours, not to exceed 6 teaspoonfuls in 24 hours
Children under 6 years of age: | Consult a doctor.

Other information

Store at 59° - 86°F (15° - 30°C)

Inactive ingredients

Citric Acid, Flavor, Methylparaben, Potassium Citrate, Propylene Glycol, Propylparaben, Purified water, Sucralose,Sorbitol

Questions? Comments?

Serious side effects associated with use of this product may be reported to this number.
Call 1-800-882-1041
Mon. - Fri. (8 a.m. to 5 p.m. CST).